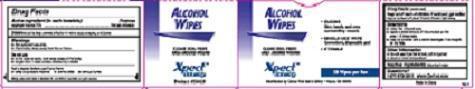 DRUG LABEL: ALCOHOL WIPE
NDC: 42961-504 | Form: SWAB
Manufacturer: Cintas Corporation
Category: otc | Type: HUMAN OTC DRUG LABEL
Date: 20140225

ACTIVE INGREDIENTS: ISOPROPYL ALCOHOL 0.70 g/1 mL
INACTIVE INGREDIENTS: WATER

Drug Facts

Active Ingredients

Isopropyl Alcohol 70%

Purpose

first aid antiseptic

Directions

Clean the affected area

apply a small amount of this product on the area 1-3 times daily

may be covered with a sterile bandage. If bandaged, let dry first.

Warnings

For external use only

Flammable, Keep away from fire or flame

Do Not Use

- In the Eyes or apply over large areas of the body
- Longer than 1 week unless directed by a doctor

Stop Use

and ask a doctor if condition persists or gets worse

Keep out of reach of children

If swallowed, get medical help or contact a Poison Control Center right away.

Uses

First aid to help prevent infection in minor cuts, scrapes, and burns

Ask a doctor before use if you have

deep or puncture wounds

animal bites

serious burns

Inactive Ingredients

water

Other information

do not use if packet is torn, cut or opened

store at room temperature